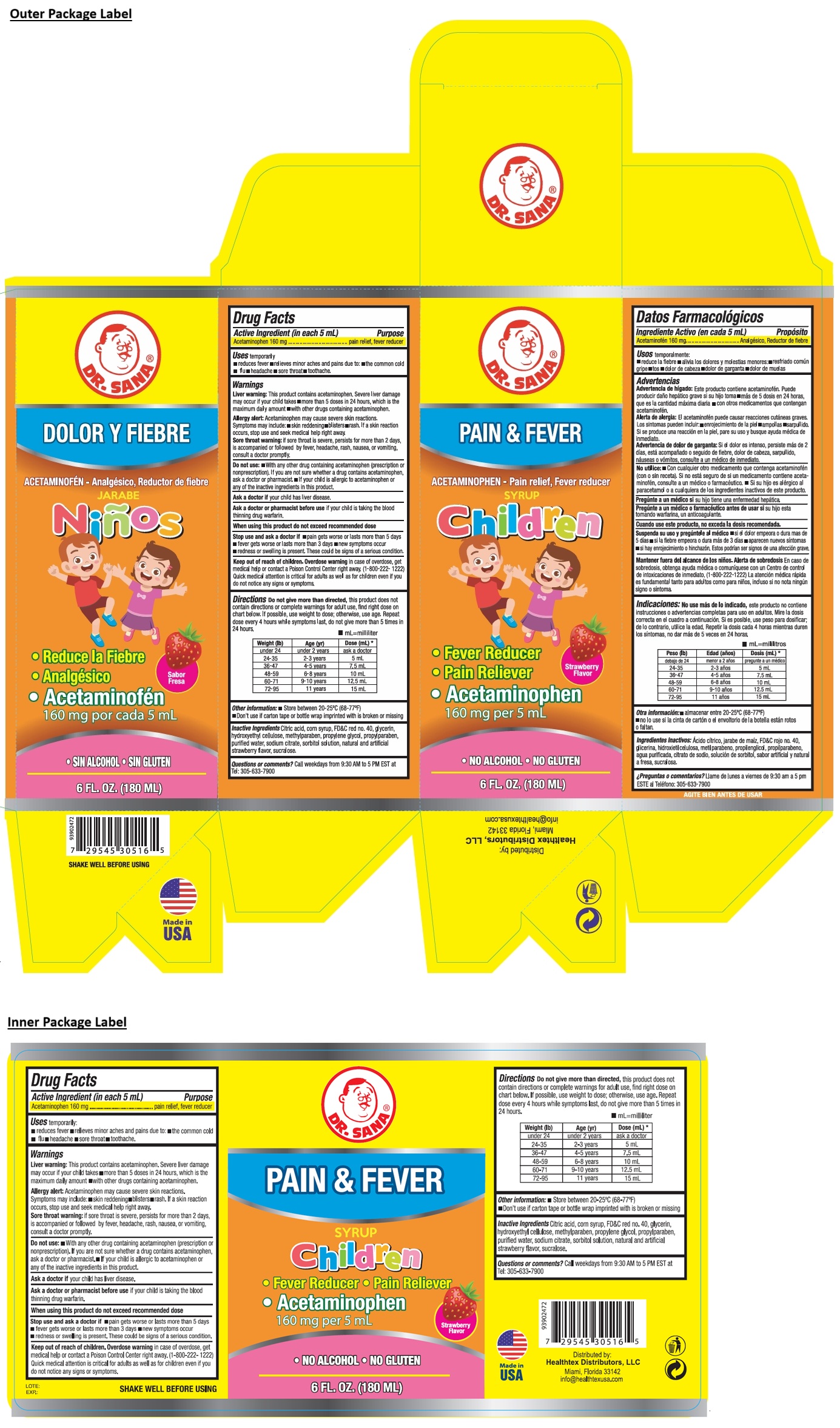 DRUG LABEL: DR. SANA PAIN AND FEVER FOR Children
NDC: 53113-516 | Form: SYRUP
Manufacturer: GADAL Laboratories, Inc
Category: otc | Type: HUMAN OTC DRUG LABEL
Date: 20250723

ACTIVE INGREDIENTS: ACETAMINOPHEN 160 mg/5 mL
INACTIVE INGREDIENTS: CITRIC ACID MONOHYDRATE; CORN SYRUP; FD&C RED NO. 40; GLYCERIN; HYDROXYETHYL CELLULOSE, UNSPECIFIED; METHYLPARABEN; PROPYLENE GLYCOL; PROPYLPARABEN; WATER; SODIUM CITRATE, UNSPECIFIED FORM; SORBITOL SOLUTION; SUCRALOSE

DR. SANA® PAIN & FEVER SYRUP Children

Active Ingredient (in each 5 mL)

Acetaminophen 160 mg

Purpose

pain relief, fever reducer

Uses

temporarily:
• reduces fever • relieves minor aches and pains due to: • the common cold • flu • headache • sore throat • toothache.

Warnings

Liver warning: This product contains acetaminophen. Severe liver damage may occur if your child takes • more than 5 doses in 24 hours, which is the maximum daily amount • with other drugs containing acetaminophen.

Allergy alert: Acetaminophen may cause severe skin reactions. Symptoms may include: • skin reddening • blisters • rash. If a skin reaction occurs, stop use and seek medical help right away.

Sore throat warning: if sore throat is severe, persists for more than 2 days, is accompanied or followed by fever, headache, rash, nausea, or vomiting, consult a doctor promptly.

Do not use: • With any other drug containing acetaminophen (prescription or nonprescription). If you are not sure whether a drug contains acetaminophen, ask a doctor or pharmacist. • If your child is allergic to acetaminophen or any of the inactive ingredients in this product.

Ask a doctor if your child has liver disease.

Ask a doctor or pharmacist before use if your child is taking the blood thinning drug warfarin.

When using this product do not exceed recommended dose

Stop use and ask a doctor if • pain gets worse or lasts more than 5 days • fever gets worse or lasts more than 3 days • new symptoms occur • redness or swelling is present. These could be signs of a serious condition.

Keep out of reach of children. Overdose warning in case of overdose, get medical help or contact a Poison Control Center right away. (1-800-222-1222) Quick medical attention is critical for adults as well as for children even if you do not notice any signs or symptoms.

Directions

Do not give more than directed, this product does not contain directions or complete warnings for adult use, find right dose on chart below. If possible, use weight to dose; otherwise, use age. Repeat dose every 4 hours while symptoms last, do not give more than 5 times in 24 hours.

• mL=milliliter

Weight (lb) | Age (yr) | Dose (mL) *
under 24 | under 2 years | ask a doctor
24-35 | 2-3 years | 5 mL
36-47 | 4-5 years | 7.5 mL
48-59 | 6-8 years | 10 mL
60-71 | 9-10 years | 12.5 mL
72-95 | 11 years | 15 mL

Other information:

• Store between 20-25℃ (68-77˚F)
• Don't use if carton tape or bottle wrap imprinted with is broken or missing

Inactive Ingredients

Citric acid, corn syrup, FD&C red no. 40, glycerin, hydroxyethyl cellulose, methylparaben, propylene glycol, propylparaben, purified water, sodium citrate, sorbitol solution, natural and artificial strawberry flavor, sucralose.

Questions or comments?

Call weekdays from 9:30 AM to 5 PM EST at Tel: 305-633-7900

• Fever Reducer
• Pain Reliever

• NO ALCOHOL • NO GLUTEN

SHAKE WELL BEFORE USING

Distributed by:

Healthtex Distributors, LLC
Miami, Florida 33142
info@healthtexusa.com

Made in USA